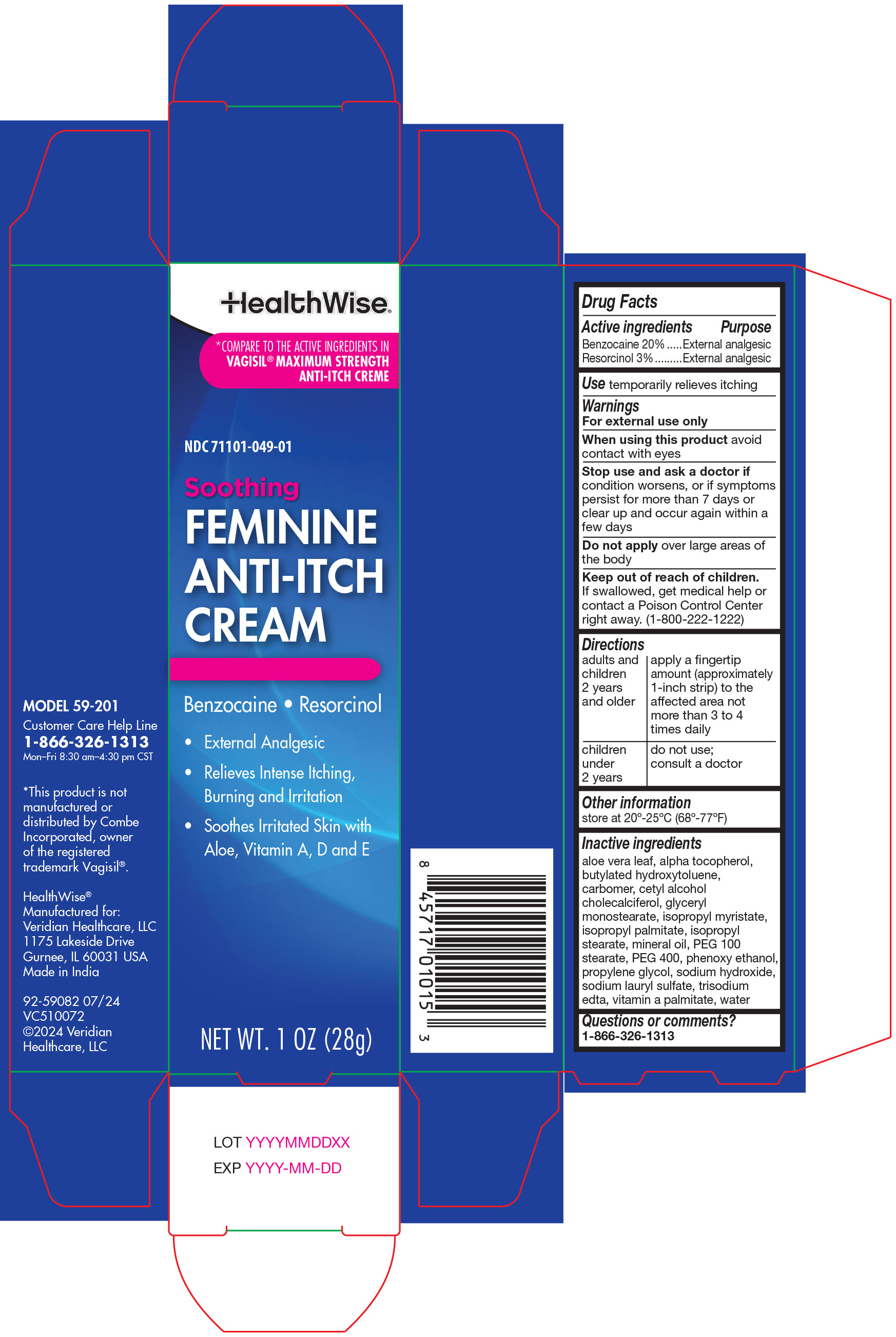 DRUG LABEL: HealthWise Feminine Anti-Itch Cream
NDC: 71101-049 | Form: CREAM
Manufacturer: Veridian Healthcare
Category: otc | Type: HUMAN OTC DRUG LABEL
Date: 20251002

ACTIVE INGREDIENTS: BENZOCAINE 5.67 g/28 g; RESORCINOL 0.85 g/28 g
INACTIVE INGREDIENTS: CARBOMER HOMOPOLYMER TYPE C (ALLYL PENTAERYTHRITOL CROSSLINKED); CETYL ALCOHOL; CHOLECALCIFEROL; GLYCERYL MONOSTEARATE; ISOPROPYL MYRISTATE; ISOPROPYL PALMITATE; ISOPROPYL STEARATE; BUTYLATED HYDROXYTOLUENE; POLYETHYLENE GLYCOL 4000; MINERAL OIL; PEG-100 STEARATE; PROPYLENE GLYCOL; WATER; ALOE VERA LEAF; VITAMIN A PALMITATE; SODIUM HYDROXIDE; SODIUM LAURYL SULFATE; ALPHA-TOCOPHEROL; EDETATE TRISODIUM; PHENOXYETHANOL

HealthWise Feminine Anti-Itch Cream

Drug Facts Active ingredients

Benzocaine 20%
Resorcinol 3%

Purpose

External analgesic

Keep out of reach of children

If swallowed, get medical help or contact a Poison Control Center right away. (1-800-222-1222)

Use

temporarily relieves itching

Warnings

For external use only

When using this product

avoid contact with the eyes

Stop use and ask a doctor if

condition worsens, or if symptoms persist for more than 7 days or clear up and occur again within a few days

Directions

Do not apply over large area of the body.

adults and children 12 years and older: apply a fingertip amount (approximately 1-inch strip) to the affected area not more than 3 to 4 times daily

children under 12 years: do not use; consult a doctor

Other Information

store at 20° -25° C (68° -77° F)

Questions or comments?

1-866-326-1313